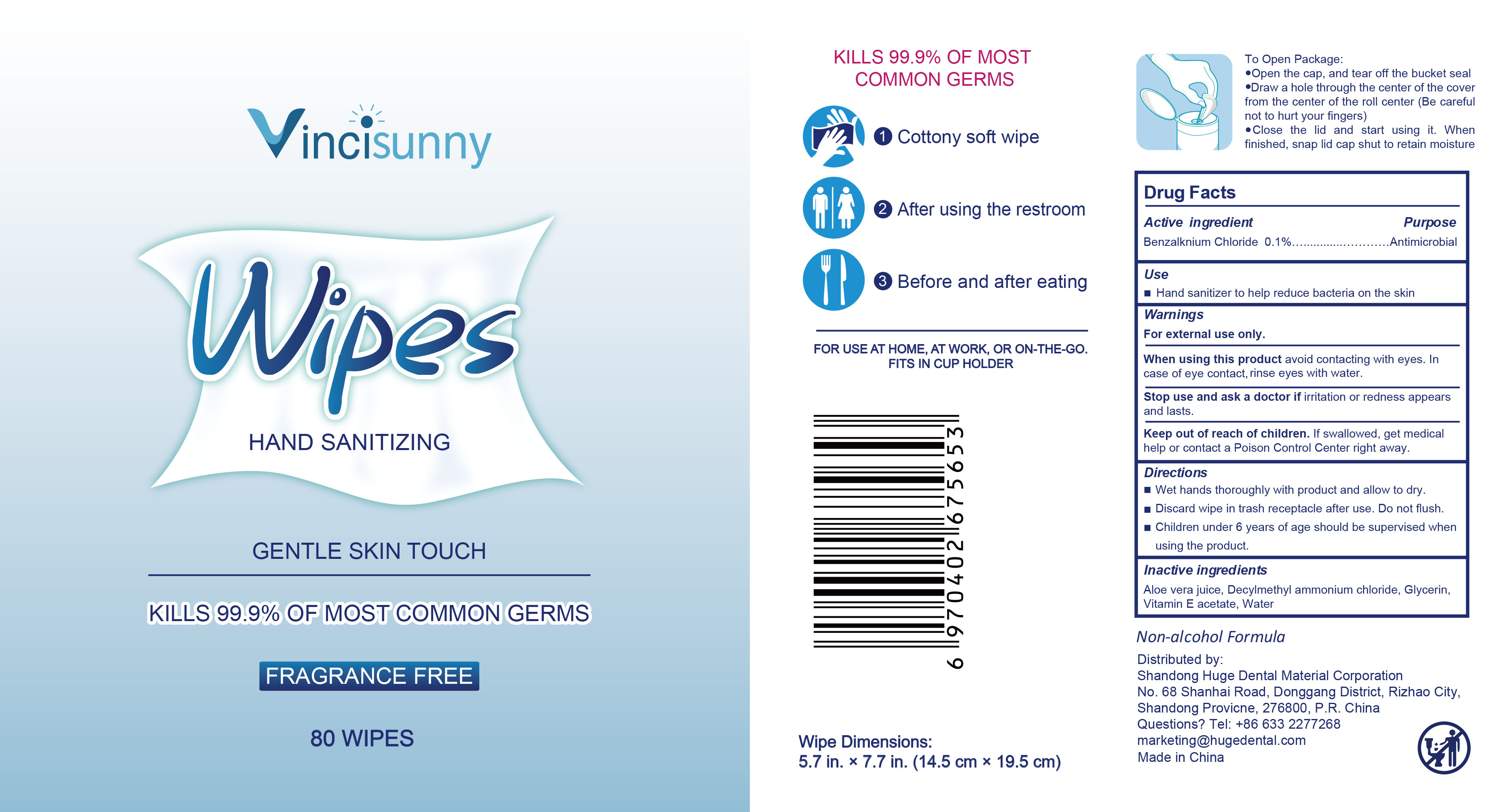 DRUG LABEL: Vincisunny Hand Sanitizing Wipes
NDC: 73718-002 | Form: CLOTH
Manufacturer: Shandong Huge Dental Material Corporation
Category: otc | Type: HUMAN OTC DRUG LABEL
Date: 20200405

ACTIVE INGREDIENTS: BENZALKONIUM CHLORIDE 0.1 mg/100 mL
INACTIVE INGREDIENTS: WATER

Hand Sanitizing Wipes NDC

Indications and usage

Hand sanitizer to help reduce bacteria on the skin.

Purpose

Antimicrobial

Active ingredient

Benzalknium Chloride 0.1%

Inactive ingredients

Aloe vera juice, Decylmethyl ammonium chloride, Glycerin, Vitamin E acetate, Water

Dosage and administration

Dosage: CLOTH

Administration: TOPICAL

Warnings

For external use only.
When using this product avoid contacting with eyes. In case of eye contact, rinse eyes with water.
Stop use and ask a doctor if irritation or redness appears and lasts.

Keep out of reach of children. If swallowed, get medical help or contact a Poison Control Center right away.